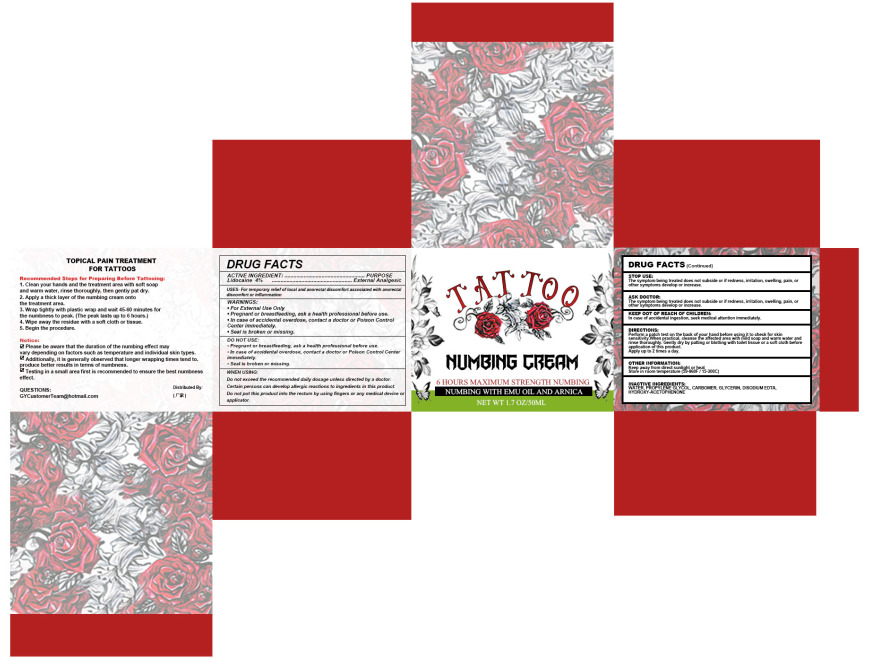 DRUG LABEL: tattoo cream
NDC: 84322-004 | Form: CREAM
Manufacturer: Shenzhen Gaoye E-commerce Co., Ltd
Category: otc | Type: HUMAN OTC DRUG LABEL
Date: 20240729

ACTIVE INGREDIENTS: LIDOCAINE 4 g/100 mL
INACTIVE INGREDIENTS: WATER; PROPYLENE GLYCOL; CARBOMER HOMOPOLYMER, UNSPECIFIED TYPE; GLYCERIN; EDETATE DISODIUM; 3'-HYDROXYACETOPHENONE

84322-004

Active Ingredient(s)

Lidocaine 4%

Purpose

External Analgesic

Use

For temporary relief of local and anorectal discomfort associated with anorectal discomfort or inflammation

Warnings

• For External Use Only

• Pregnant or breastfeeding, ask a health professional before use.

• In case of accidental overdose, contact a doctor or Poison Control Center immediately.

• Seal is broken or missing.

Do not use

• Pregnant or breastfeeding, ask a health professional before use.

• In case of accidental overdose, contact a doctor or Poison Control Center immediately.

• Seal is broken or missing.

WHEN USING

Do not exceed the recommended daily dosage unless directed by a doctor. Certain persons can develop allergic

reactions to ingredients in this product. Do not put this product into the rectum by using fingers or any medical

device or applicator.

STOP USE

The symptom being treated does not subside or if redness, irritation, swelling, pain, or other symptoms develop or increase.

KEEP OUT OF REACH OF CHILDREN

In case of accidental ingestion, seek medical attention immediately.

Directions

Perform a patch test on the back of your hand before using it to check for skin

sensitivity.When practical, cleanse the affected area with mild soap and warm water and

rinse thoroughly. Gently dry by patting or blotting with toilet tissue or a soft cloth before

application of this product.

Apply up to 2 times a day.

Other information

Keep away from direct sunlight or heat

Store in room temperature (59-860F / 15-300C)

Inactive ingredients

WATER PROPYLENE GLYCOL, CARBOMER, GLYCERIN, DISODIUM EDTA. HYDROXY-ACETOPHENONE